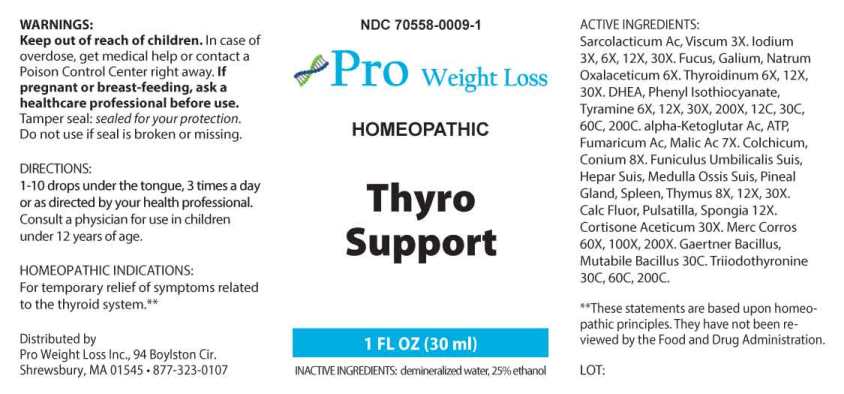 DRUG LABEL: Thyro Support
NDC: 70558-0009 | Form: LIQUID
Manufacturer: Pro Weight Loss Inc.
Category: homeopathic | Type: HUMAN OTC DRUG LABEL
Date: 20250108

ACTIVE INGREDIENTS: LACTIC ACID, L- 3 [hp_X]/1 mL; VISCUM ALBUM FRUITING TOP 3 [hp_X]/1 mL; IODINE 3 [hp_X]/1 mL; FUCUS VESICULOSUS 6 [hp_X]/1 mL; GALIUM APARINE WHOLE 6 [hp_X]/1 mL; SODIUM DIETHYL OXALACETATE 6 [hp_X]/1 mL; THYROID 6 [hp_X]/1 mL; PRASTERONE 6 [hp_X]/1 mL; PHENYL ISOTHIOCYANATE 6 [hp_X]/1 mL; TYRAMINE 6 [hp_X]/1 mL; ADENOSINE TRIPHOSPHATE DISODIUM 7 [hp_X]/1 mL; .ALPHA.-KETOGLUTARIC ACID 7 [hp_X]/1 mL; FUMARIC ACID 7 [hp_X]/1 mL; MALIC ACID 7 [hp_X]/1 mL; COLCHICUM AUTUMNALE BULB 8 [hp_X]/1 mL; CONIUM MACULATUM FLOWERING TOP 8 [hp_X]/1 mL; SUS SCROFA UMBILICAL CORD 8 [hp_X]/1 mL; PORK LIVER 8 [hp_X]/1 mL; SUS SCROFA BONE MARROW 8 [hp_X]/1 mL; SUS SCROFA PINEAL GLAND 8 [hp_X]/1 mL; SUS SCROFA SPLEEN 8 [hp_X]/1 mL; SUS SCROFA THYMUS 8 [hp_X]/1 mL; CALCIUM FLUORIDE 12 [hp_X]/1 mL; PULSATILLA PRATENSIS WHOLE 12 [hp_X]/1 mL; SPONGIA OFFICINALIS SKELETON, ROASTED 12 [hp_X]/1 mL; CORTISONE ACETATE 30 [hp_X]/1 mL; MERCURIC CHLORIDE 60 [hp_X]/1 mL; SALMONELLA ENTERICA SUBSP. ENTERICA SEROVAR ENTERITIDIS 30 [hp_C]/1 mL; ESCHERICHIA COLI 30 [hp_C]/1 mL; LIOTHYRONINE 30 [hp_C]/1 mL
INACTIVE INGREDIENTS: WATER; ALCOHOL

DRUG FACTS:

ACTIVE INGREDIENTS:

Sarcolacticum Acidum 3X, Viscum Album 3X, Iodium 3X, 6X, 12X, 30X, Fucus Vesiculosus 6X, Galium Aparine 6X, Natrum Oxalaceticum 6X, Thyroidinum (Suis) 6X, 12X, 30X, DHEA (Dehydroepiandrosterone) 6X, 12X, 30X, 200X, 12C, 30C, 60C, 200C, Phenyl Isothiocyanate 6X, 12X, 30X, 200X, 12C, 30C, 60C, 200C, Tyramine 6X, 12X, 30X, 200X, 12C, 30C, 60C, 200C, Adenosinum Triphosphoricum Dinatrum 7X, alpha-Ketoglutaricum Acidum 7X, Fumaricum Acidum, 7X Malic Acidum 7X, Colchicum Autumnale 8X, Conium Maculatum 8X, Funiculus Umbilicalis Suis 8X, 12X, 30X, Hepar Suis 8X, 12X, 30X, Medulla Ossis Suis 8X, 12X, 30X, Pineal Gland (Suis) 8X, 12X, 30X, Spleen (Suis) 8X, 12X, 30X, Thymus (Suis) 8X, 12X, 30X, Calcarea Fluorica 12X, Pulsatilla (Pratensis) 12X, Spongia Tosta 12X, Cortisone Aceticum 30X, Mercurius Corrosivus 60X, 100X, 200X, Gaertner Bacillus (Bach) 30C, Mutabile Bacillus (Bach) 30C, Triiodothyronine 30C, 60C, 200C.

HOMEOPATHIC INDICATIONS:

For temporary relief of symptoms related to the thyroid system.**

**These statements are based upon homeopathic principles. They have not been reviewed by the Food and Drug Administration.

WARNINGS:

Keep out of reach of children. In case of overdose, get medical help or contact a Poison Control Center right away.

If pregnant or breast-feeding, ask a health professional before use.

Tamper seal: "Sealed for Your Protection." Do not use if seal is broken or missing.

Keep out of reach of children. In case of overdose, get medical help or contact a Poison Control Center right away.

DIRECTIONS:

1-10 drops under the tongue, 3 times a day or as directed by your health professional. Consult a physician for use in children under 12 years of age.

HOMEOPATHIC INDICATIONS:

For temporary relief of symptoms related to the thyroid system.**

**These statements are based upon homeopathic principles. They have not been reviewed by the Food and Drug Administration.

INACTIVE INGREDIENTS:

demineralized water, 25% ethanol

QUESTIONS:

Distributed by

Pro Weight Loss Inc., 94 Boylston Cir.

Shrewsbury, MA 01545 • 877-323-0107

PACKAGE LABEL DISPLAY:

NDC 70558-0009-1

Pro Weight Loss

HOMEOPATHIC

THYRO SUPPORT

1 FL OZ (30 ml)